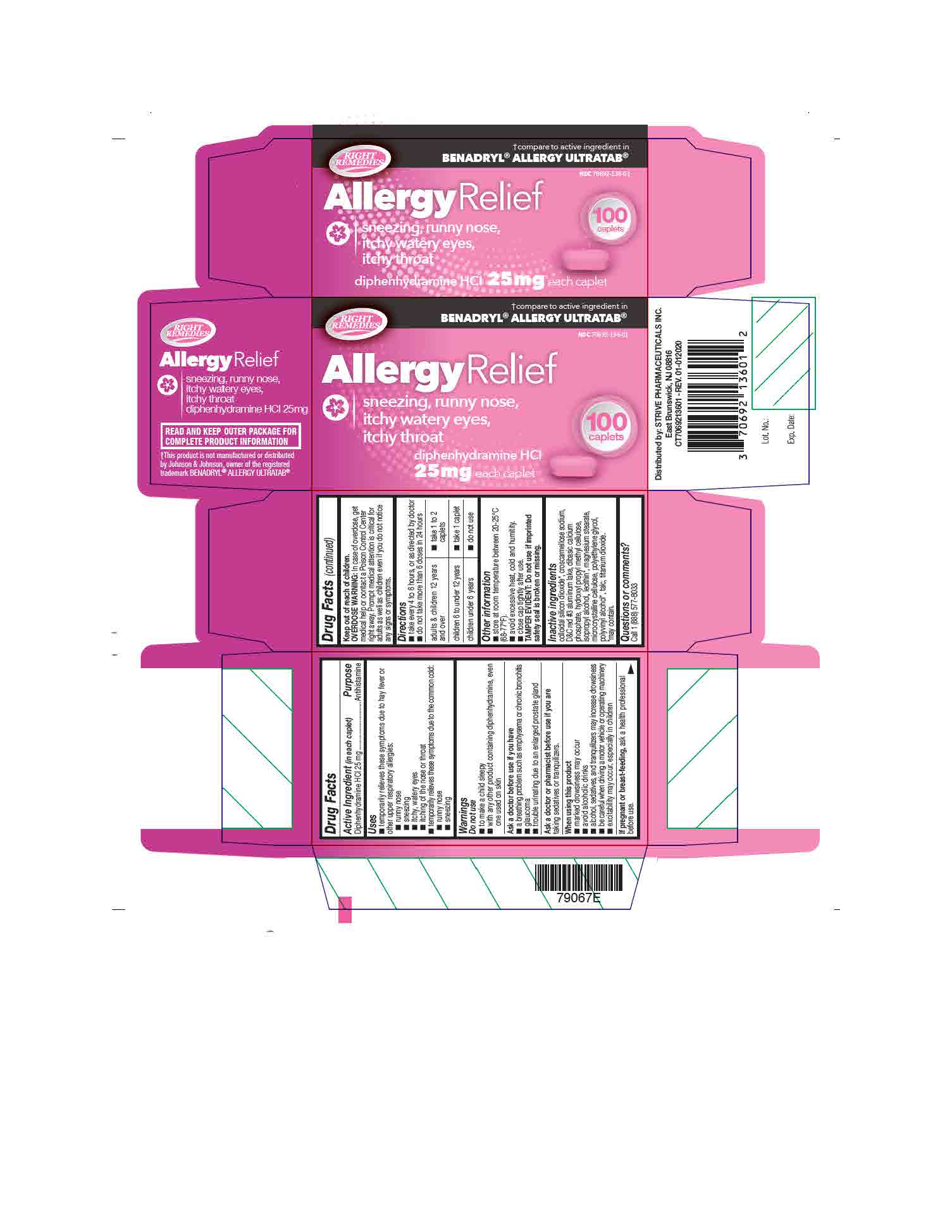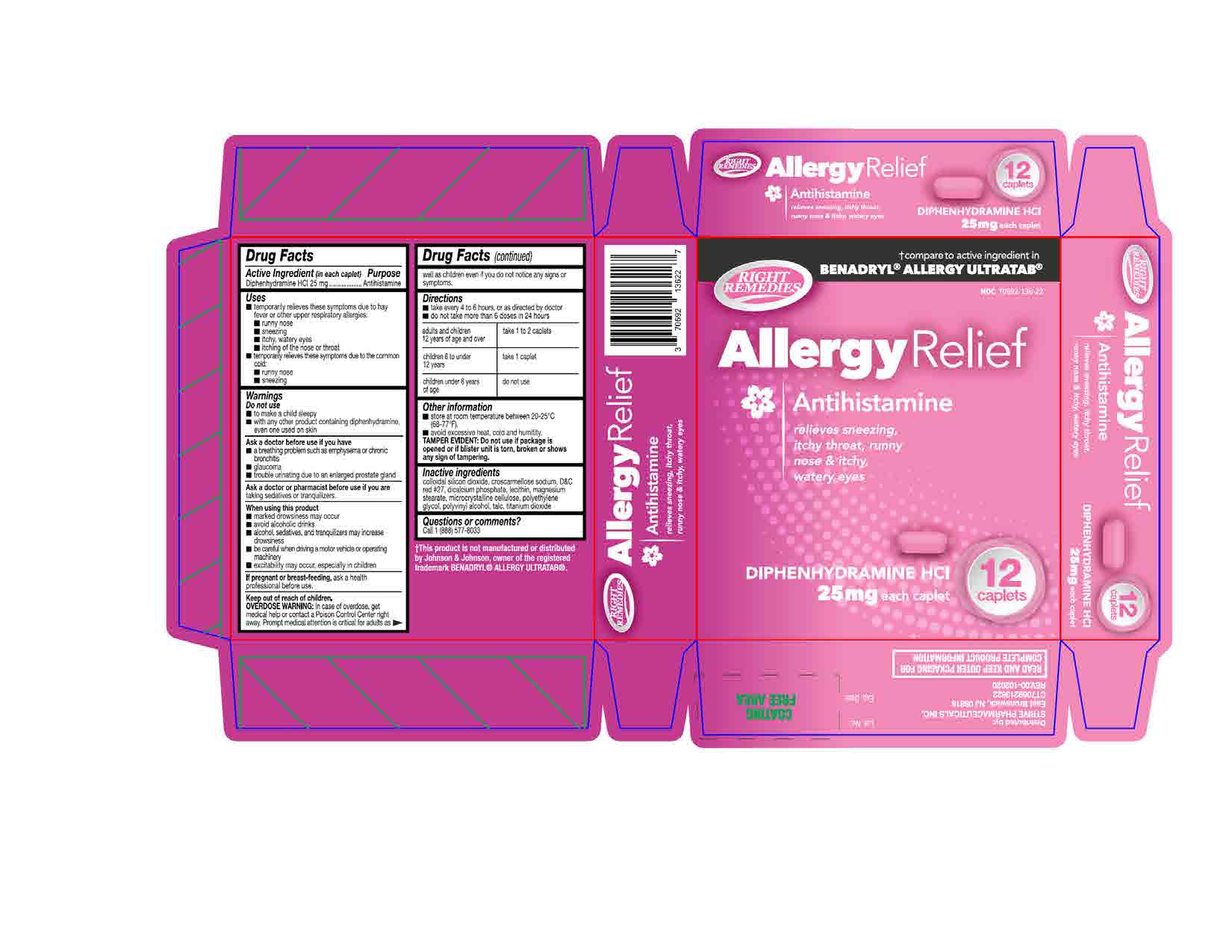 DRUG LABEL: Diphenhydramine Hydrochloride 25mg
NDC: 70692-136 | Form: TABLET
Manufacturer: Strive Pharmaceuticals Inc
Category: otc | Type: HUMAN OTC DRUG LABEL
Date: 20220412

ACTIVE INGREDIENTS: DIPHENHYDRAMINE HYDROCHLORIDE 25 mg/1 1
INACTIVE INGREDIENTS: CROSCARMELLOSE SODIUM; POLYVINYL ALCOHOL, UNSPECIFIED; TALC; POLYETHYLENE GLYCOL, UNSPECIFIED; MAGNESIUM STEARATE; TITANIUM DIOXIDE; SILICON DIOXIDE; CELLULOSE, MICROCRYSTALLINE; D&C RED NO. 27; CALCIUM PHOSPHATE, DIBASIC, ANHYDROUS; LECITHIN, SOYBEAN

Allergy Relief Caplet
(Diphenhydramine HCl 25mg) - Pink caplet

ACTIVE INGREDIENT

Diphenhydramine HCl 25mg

INACTIVE INGREDIENT

colloidal silicon dioxide, croscarmellose sodium, D&C red #27, dicalcium phosphate, lecithin, magnesium stearate, microcrystalline cellulose, polyethylene glycol, polyvinyl alcohol, talc, titanium dioxide

DOSAGE AND ADMINISTRATION

- take every 4 to 6 hours, or as directed by a doctor
- do not take more than 6 doses in 24 hours

adults and children 12 years of age and over | take 1 to 2 caplets
children 6 to under 12 years | take 1 caplet
children under 6 years of age | do not use

INDICATIONS AND USAGE

temporarily relieves these symptoms due to hay fever or other upper respiratory allergies:

- runny nose
- sneezing
- itchy, watery eyes
- itching of the nose or throat

temporarily relieves these symptoms due to the common cold:

- runny nose
- sneezing

Do not use

- to make a child sleepy
- with any other product containing diphenhydramine, even one used on skin

Ask a doctor before use if you have

- a breathing problem such as emphysema or chronic bronchitis
- glaucoma
- trouble urinating due to an enlarged prostrate gland

Ask a doctor or a pharmacist before use if

you are taking sedatives or tranquilzers

When using this product

- marked drowsiness may occur
- avoid alcoholic drinks
- alcohol, sedatives, and tranquilizers may increase drowsiness
- be careful when driving a motor vehicle or operating machinery
- excitability may occur, especially in children

If pregnant or breast-feeding,

ask a health professional before use

Keep out of reach of children

Overdose warning: In case of accidental overdose, get medical help or contact a Poison Control Center right away. Prompt medical attention is critical for adults as well as for children even if you do not notice any signs or symptoms.

Keep out of reach of children

Overdose Warning: In case of accidental overdose, get medical help or contact a Poison Control Center right away. Prompt medical attention is critical for adults as well as for children even if you do not notice any signs or symptoms.

PURPOSE

Antihistamine

OTHER SAFETY INFORMATION

- store at room temperature between 20ºC - 25ºC (68ºF - 77ºF)
- avoid excessive heat, cold and humidity